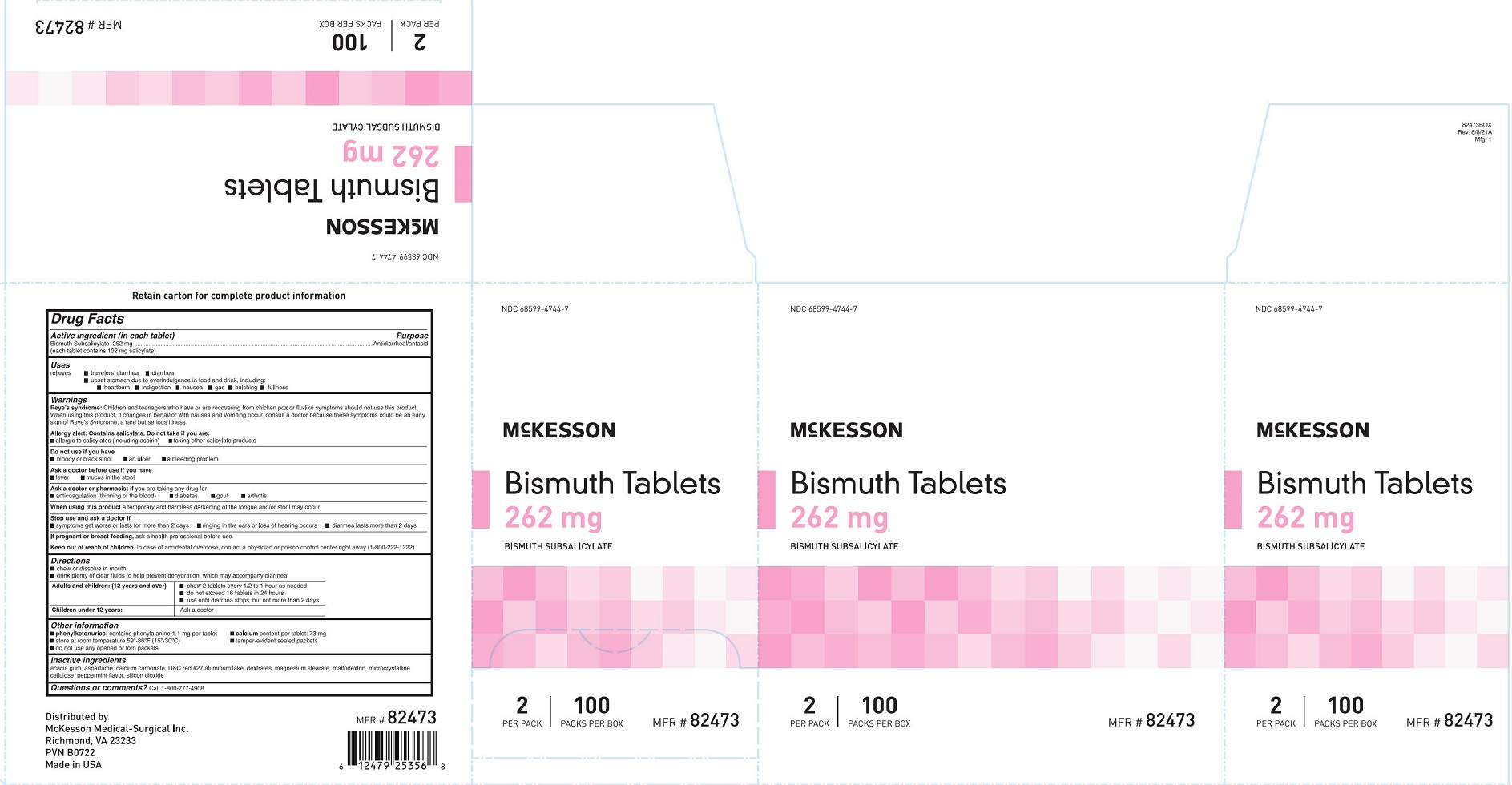 DRUG LABEL: McKesson Bismuth
NDC: 68599-4744 | Form: TABLET, CHEWABLE
Manufacturer: McKesson Medical-Surgical
Category: otc | Type: HUMAN OTC DRUG LABEL
Date: 20250908

ACTIVE INGREDIENTS: BISMUTH SUBSALICYLATE 262 mg/1 1
INACTIVE INGREDIENTS: DEXTRATES; MAGNESIUM STEARATE; SILICON DIOXIDE; MALTODEXTRIN; ACACIA; ASPARTAME; CALCIUM CARBONATE; CELLULOSE, MICROCRYSTALLINE; D&C RED NO. 27

McKesson Bismuth Tablets

Drug Facts

Active ingredient (in each tablet)

Bismuth Subsalicylate 262 mg

(each tablet contains 102 mg salicylate)

Purpose antidiarrheal/antacid

Uses

relieves

- traveler's diarrhea
- diarrhea
- upset stomach reliever due to overindulgence in food and drink, including: • heartburn • indigestion • nausea • gas • belching

• fullness

Warnings

Reye's syndrome: Children and teenagers who have or are recovering from chicken pox or flu-like symptoms should not use this product. When using this product, if changes in behavior with nausea and vomiting occur, consult a doctor because these symptoms could be an early sign of Reye's Syndrome a rare but serious illness.

Allergy alert: Contains salicylate. Do not take if you are:

- allergic to salicylates (including aspirin)
- taking other salicylate products

Do not use if you have

- bloody or black stool
- an ulcer
- a bleeding problem

Ask a doctor before use if you have

- fever
- mucus in the stool

Ask a doctor or pharmacist if you are taking any drug for

- anticoagulation (thinning of the blood)
- diabetes
- gout
- arthritis

When using this product a temporary and harmless darkening of the tongue and/or stool may occur.

Stop use and ask a doctor if

- symptoms get worse or lasts more than 2 days
- ringing in the ears or loss of hearing occurs
- diarrhea lasts more than 2 days

PREGNANCY OR BREAST FEEDING

If pregnant or breast-feeding, ask a health professional before use.

Keep out of reach of children. In case of accidental overdose, contact a physician or poison control center right away (1-800-222-1222).

Directions

- chew or dissolve in mouth
- drink plenty of clear fluids to help prevent dehydration, which may accompany diarrhea

Adults and children: (12 years and over)

- chew 2 tablets every 1/2 to 1 hour as needed
- do not exceed 16 tablets in 24 hours
- use until diarrhea stops but not more than 2 days

Children under 12 years:

Ask a doctor

Other information

- phenylketonurics: contains phenylalanine 1.1 mg per tablet
- calcium content per tablet: 73 mg
- store at room temperature 59°-86°F (15°-30°C)
- tamper-evident sealed packets
- do not use any opened or torn packets

Inactive ingredients

acacia gum, aspartame, calcium carbonate, D&C red #27 aluminum lake, dextrates, magnesium stearate, maltodextrin, microcrystalline cellulose, peppermint flavor, silicon dioxide

Questions or comments? 1-800-777-4908

PACKAGE LABEL

NDC 68599-4744-7

McKesson

Bismuth Tablets 262 mg

Bismuth Suybsalicylate

2 Per Pack | 100 Packs Per Box

MFR # 82473